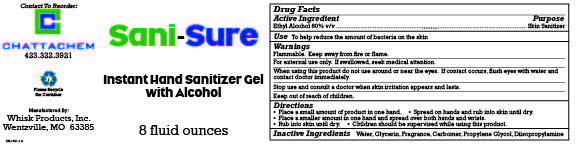 DRUG LABEL: Sani-Sure
NDC: 65585-359 | Form: GEL
Manufacturer: Whisk Products, Inc.
Category: otc | Type: HUMAN OTC DRUG LABEL
Date: 20240904

ACTIVE INGREDIENTS: ALCOHOL 600 mL/1 L
INACTIVE INGREDIENTS: WATER; GLYCERIN; CARBOMER INTERPOLYMER TYPE A (ALLYL SUCROSE CROSSLINKED); PROPYLENE GLYCOL; DIISOPROPYLAMINE

Sani-Sure

Active Ingredient

Ethyl Alcohol 60% v/v

Purpose

Skin Sanitizer

Use

To help reduce the amount of bacteria on the skin

Warnings

Flammable. Keep away from fire or flame.

For external use only. If swallowed, seek medical attention.

When using this product do not use around or near the eyes. If contact occurs, flush eyes with water and contact doctor immediately.

Stop use and consult a doctor when skin irritation appears and lasts.

Keep out of reach of children.

Directions

- Place a small amount of product in one hand.
- Spread on hands and rub into skin until dry.
- Place a smaller amount in one hand and spread over both hands and wrists.
- Rub into skin until dry.
- Children should be supervised while using this product.

Inactive Ingredients

Water, Glycerin, Fragrance, Carbomer, Propylene Glycol, Diisopropylamine